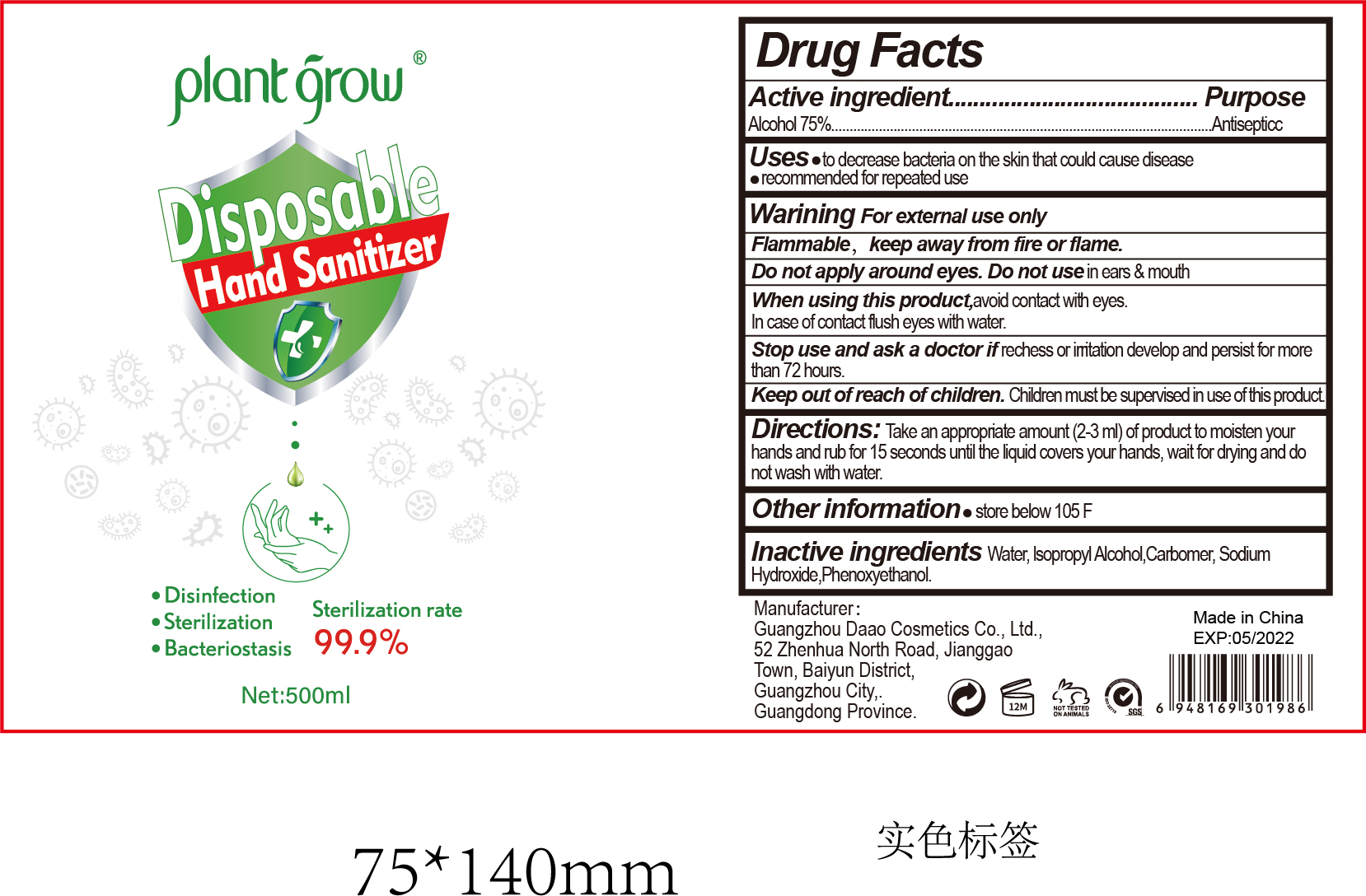 DRUG LABEL: disposable hand sanitizer
NDC: 52965-003 | Form: LIQUID
Manufacturer: Guangzhou Da'ao Cosmetics Co., Ltd
Category: otc | Type: HUMAN OTC DRUG LABEL
Date: 20200430

ACTIVE INGREDIENTS: ISOPROPYL ALCOHOL 30 mL/500 mL; ALCOHOL 305 mL/500 mL
INACTIVE INGREDIENTS: WATER; CARBOMER HOMOPOLYMER, UNSPECIFIED TYPE; TROLAMINE

ACTIVE INGREDIENT

ALCOHOL,ISOPROPANOL

PURPOSE

Disinfe ction
Sterilization
No Rinseing

INACTIVE INGREDIENT

WATER,CARBOMER,TRIETHANOLAMINE

keep out of reach of children

WARNINGS

For external use only hands

DOSAGE AND ADMINISTRATION

Flammable keep away from fire or flame

INDICATIONS AND USAGE

take an appropriate amount(2-3ml) of product to moisten your hands and rub for 15 seconds until the liquid covers your hands, wait for drying and do not wash with water.